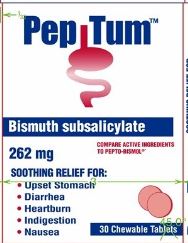 DRUG LABEL: First Aid Direct Peptum Tabs
NDC: 42961-109 | Form: TABLET, CHEWABLE
Manufacturer: Cintas Corp
Category: otc | Type: HUMAN OTC DRUG LABEL
Date: 20250929

ACTIVE INGREDIENTS: BISMUTH SUBSALICYLATE 262 mg/1 1
INACTIVE INGREDIENTS: ACACIA; ASPARTAME; CALCIUM CARBONATE; D&C RED NO. 27 ALUMINUM LAKE; DEXTRATES; MAGNESIUM STEARATE; MALTODEXTRIN; MICROCRYSTALLINE CELLULOSE; PEPPERMINT; SILICON DIOXIDE

Active ingredient (in each tablet)

Bismuth subsalicylate 262 mg

(each tablet contains 102mg salicylate)

Purpose

Antidiarrheal/Antacid

Uses

relieves

- travelers' diarrhea
- diarrhea
- upset stomach due to overindulgence in food and drink including:
- heartburn
- indigestion
- nausea
- gas
- belching
- fullness

Warnings

Reye's syndrome: Children and teenagers who have or are recovering from chicken pox or flu-like symptoms should not use this product. When using this product, if changes in behavior with nausea and vomiting occurs, consult a doctor because these symptoms could be an early sign of Reye's syndrome, a rare but serious illness.

Allergy alert: Contains salicylate. Do not take if you are

- allergic to salicylate (including asprin)
- taking other salicylate products

Do not use if you have

- an ulcer
- a bleeding problem
- bloody or black stool

Ask a doctor before use if you have

- fever
- mucus in stool

Ask a doctor or pharmacist before use if you are taking any drug for

- anticoagulation (thinning of the blood)
- diabetes
- gout
- arthritis

When using this product a temporary, but harmless darkening of the stool and/or tongue may occur

Stop use and ask a doctor if

- symptoms get worse
- ringing in the ears or loss of hearing occurs
- diarrhea lasts more than 2 days

PREGNANCY OR BREAST FEEDING

If pregnant or breast-feeding, ask a health professional before use.

Keep out of reach of children. In case of overdose, get medical help or contact a Poison Control Center (1-800-222-1222) right away.

Directions

- chew or dissolve in mouth
- Adults and children 12 years and over: 2 tablets (1 dose) every ½ hour or 4 tablets (2 doses) every hour as needed for diarrhea
- 2 tablets (1 dose) every 1/2 hour as needed for overindulgence (upset stomach, heartburn, indigestion, nausea)
- do not exceed 8 doses (16 tablets) in 24 hours
- use until diarrhea stops but not more than 2 days
- Children under 12: ask a doctor
- drink plenty of fluids to help prevent dehydration which may accompany diarrhea

Other information

- Phenylketonurics: contains phenylalanine 1.1 mg per tablet

Calcium content per tablet: 73mg

- store at room temperature 15° - 30°C (59° - 86°F)
- avoid excessive heat (over 40°C or 104°F)
- do not use if cellophane unit is torn

Inactive ingredients

acacia gum, aspartame, calcium carbonate, D&C red #27 aluminum lake, dextrates, magnesium stearate, maltodextrin, microcrystalline cellulose, peppermint flavor, silicon dioxide

Questions?

1-800-327-2704 Monday-Friday 8:00am - 5:00pm (CDT)

Principal Display Panel - Box

Pep Tum™

Bismuth subsalicylate

COMPARE ACTIVE INGREDIENTS TO PEPTO-BISMOL®*

262 mg

SOOTHING RELIEF FOR:

- Upset Stomach
- Diarrhea
- Heartburn
- Indigestion
- Nausea

30 Chewable Tablets